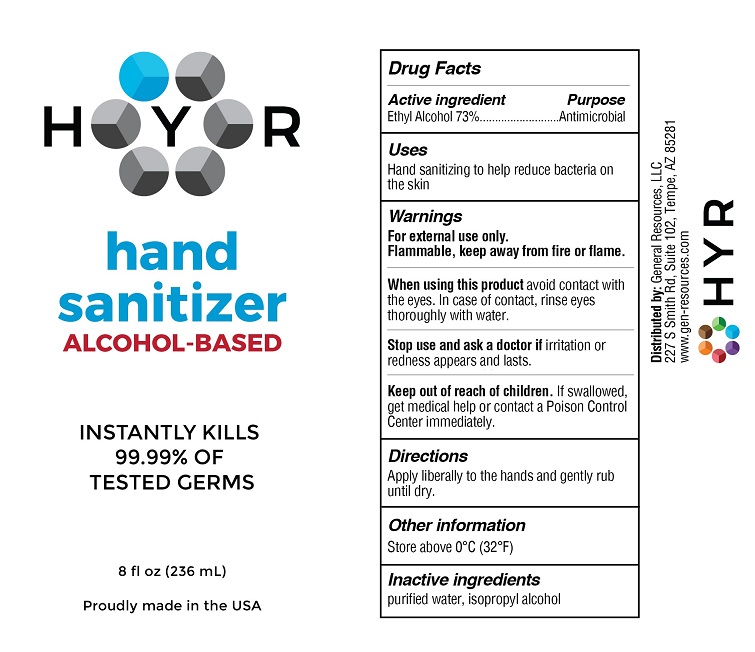 DRUG LABEL: HYR Hand Sanitizer
NDC: 70481-311 | Form: LIQUID
Manufacturer: General Resources LLC
Category: otc | Type: HUMAN OTC DRUG LABEL
Date: 20201015

ACTIVE INGREDIENTS: ALCOHOL 73 mL/100 mL
INACTIVE INGREDIENTS: WATER; ISOPROPYL ALCOHOL

HYR Hand Sanitizer Alcohol

Drug Facts

Active ingredient

Ethyl Alcohol 73%

Purpose

Antimicrobial

Uses

Hand sanitizing to help reduce bacteria on the skin

Warnings

For external use only.

Flammable. Keep away from fire or flame.

When using this product avoid contact with the eyes. In case of contact, rinse eyes thoroughly with water.

Stop use and ask a doctor if irritation or redness appears and lasts

Keep out of reach of children. If swallowed, get medical help or contact a Poison Control Center immediately.

Directions

Apply liberally to hands and gently rub until dry.

Other information

Store above 0°C (32°F)

Inactive ingredients

purified water, isopropyl alcohol

Distributed by: General Resources, LLC

227 S. Smith Road, Suite 102, Tempe, AZ 85281

www.gen-resources.com

PACKAGE LABEL

HYR

hand sanitizer

ALCOHOL-BASED

INSTANTLY KILLS 99.99% OF TESTED GERMS

8 fl oz (236 mL)

Proudly made in the USA